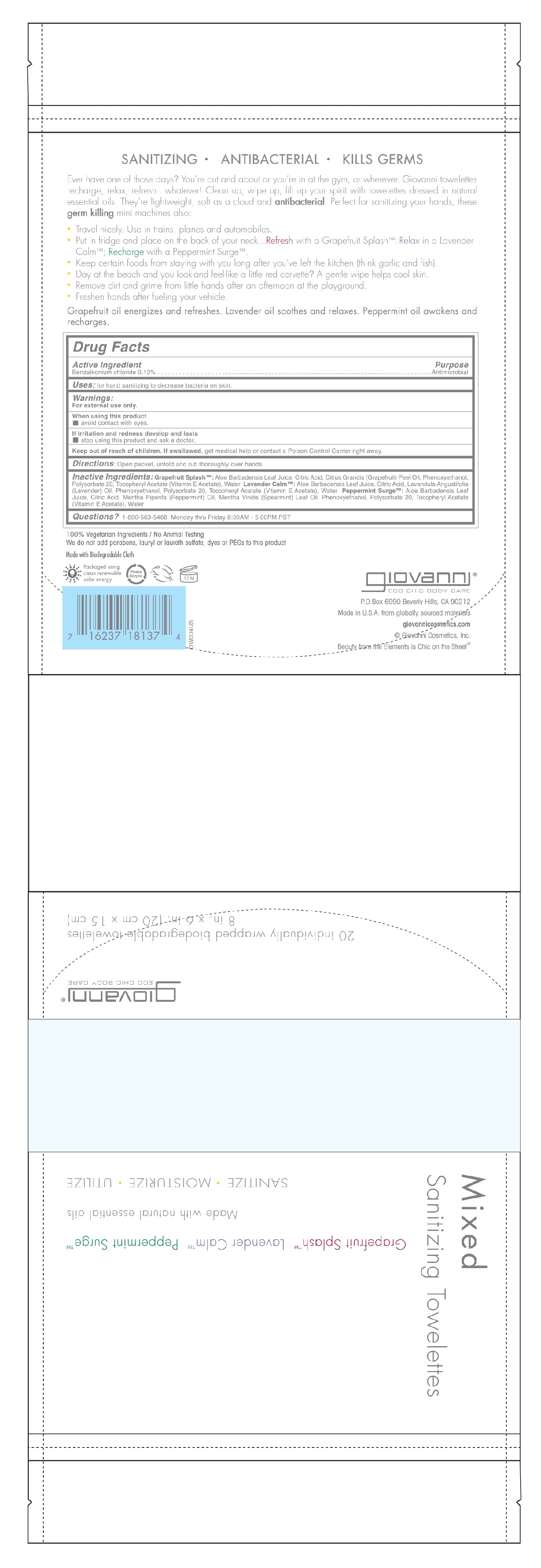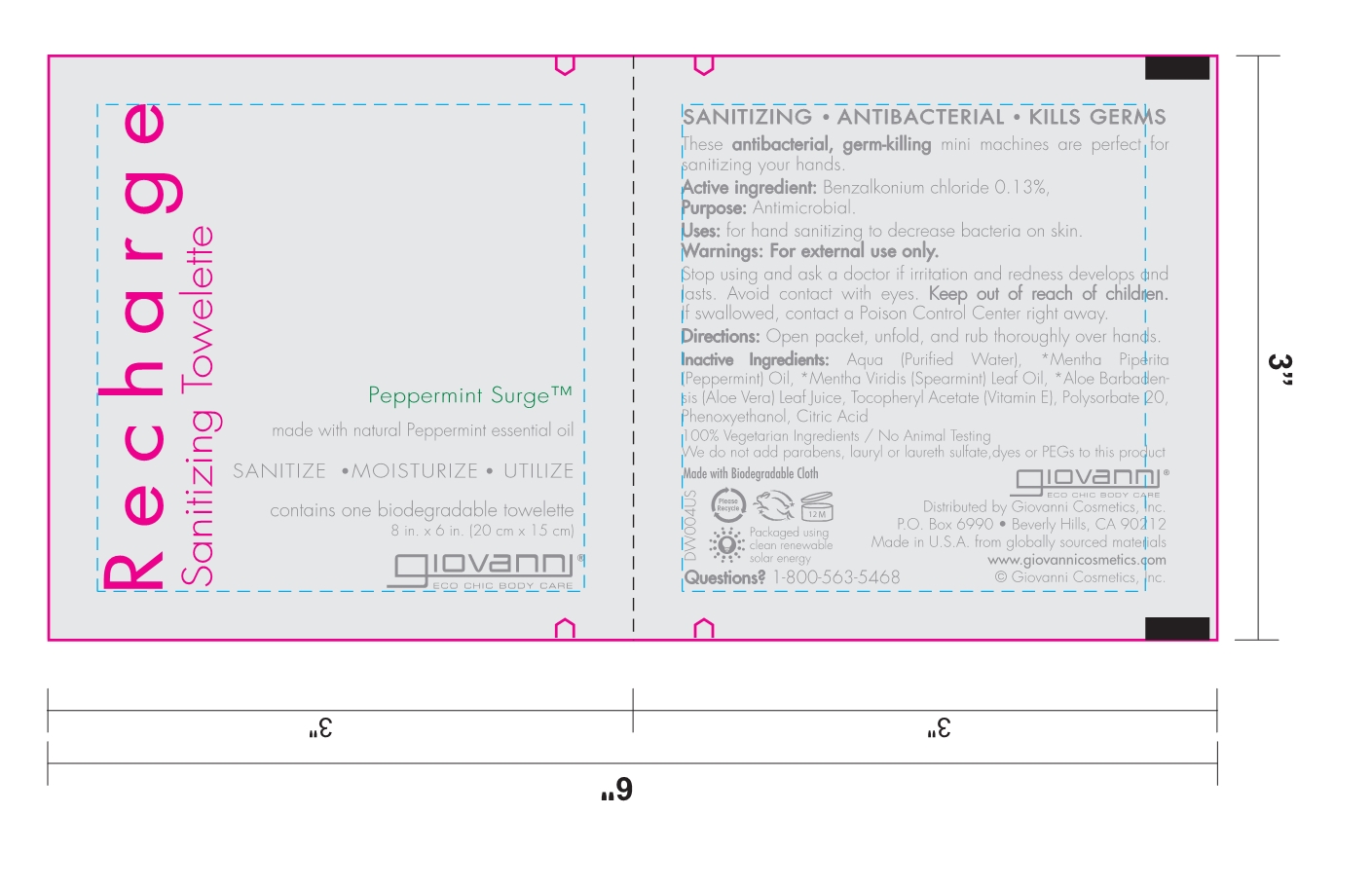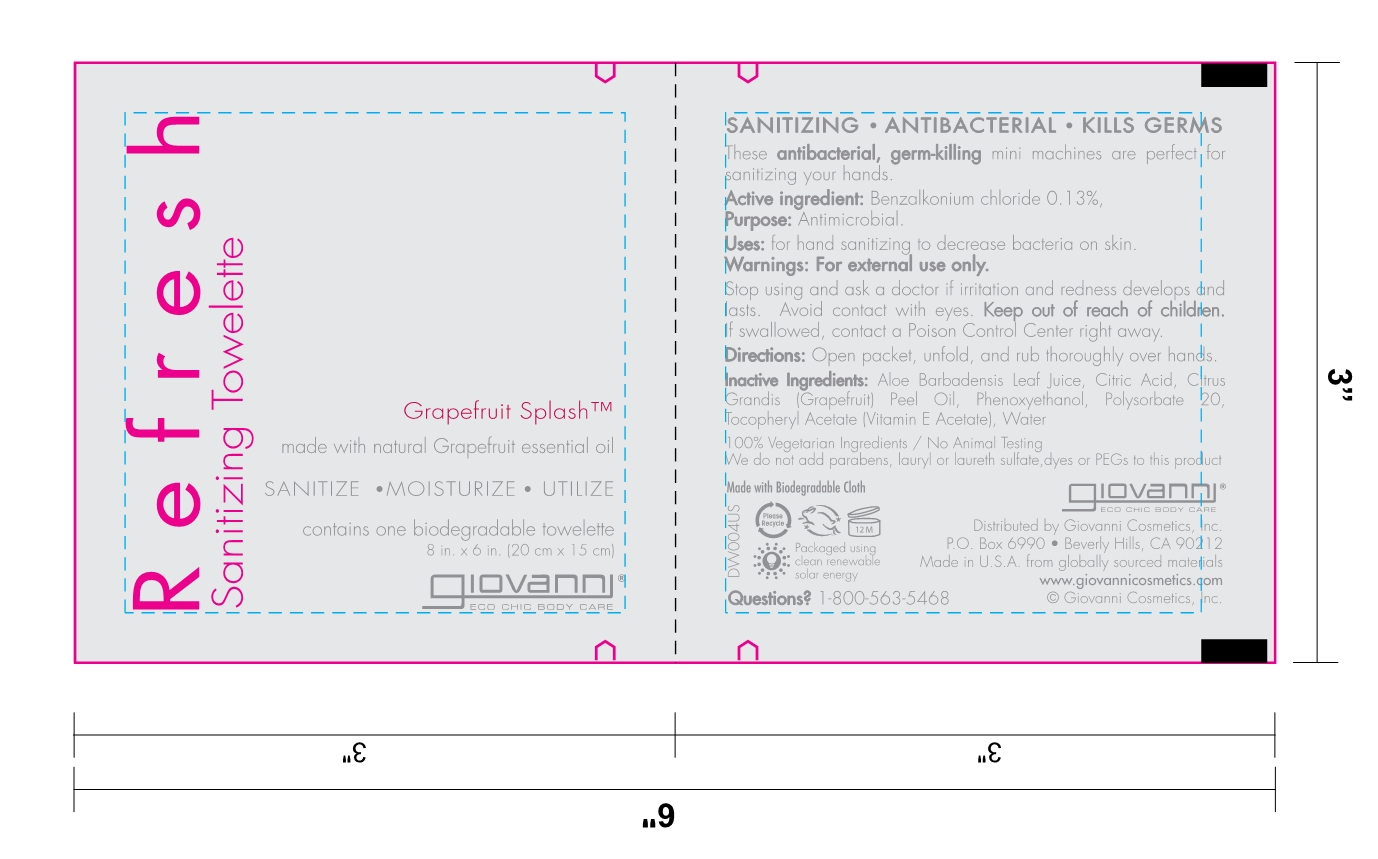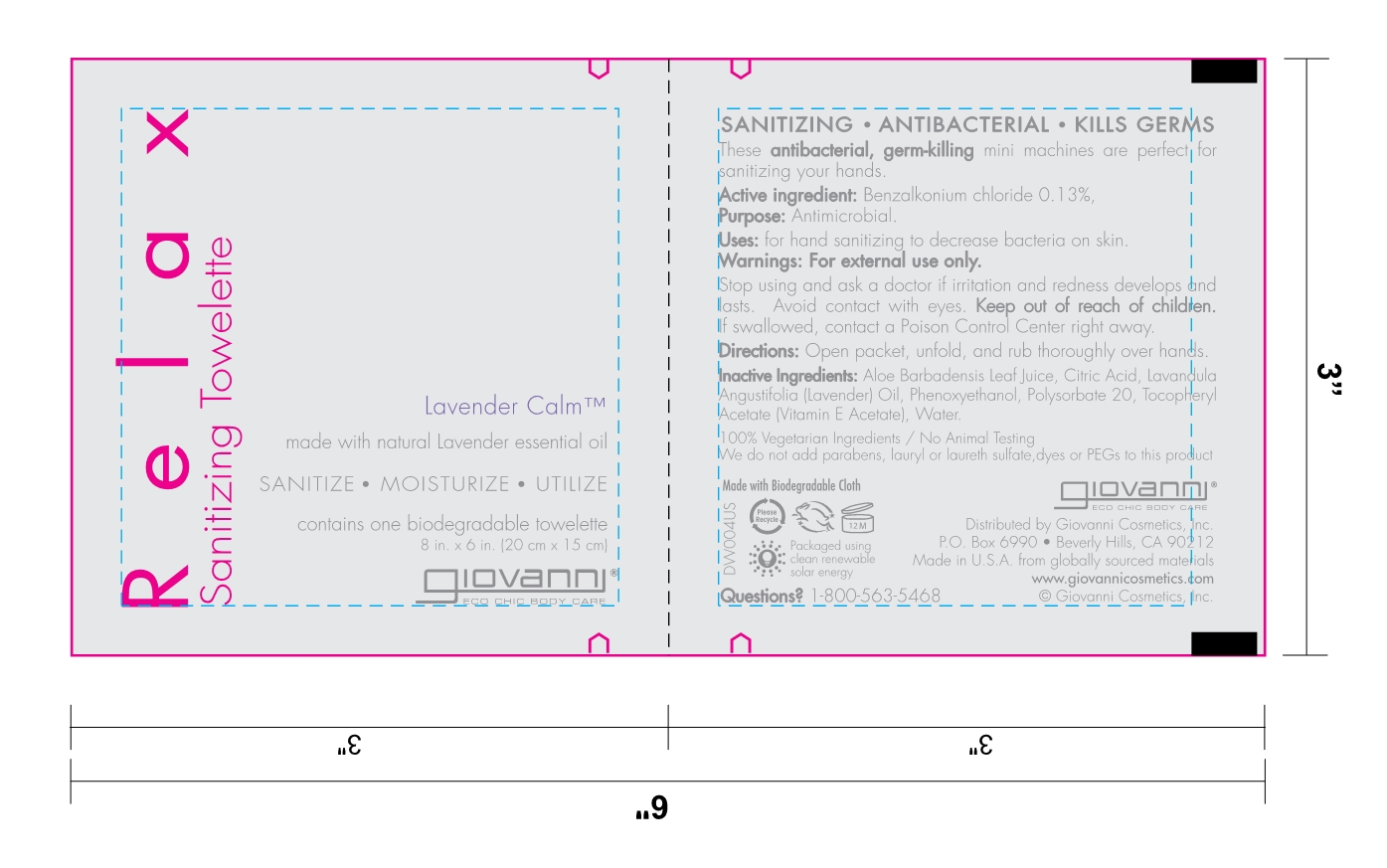 DRUG LABEL: Mixed Sanitizing Towlettes
NDC: 45942-1632 | Form: KIT | Route: TOPICAL
Manufacturer: GIOVANNI COSMETICS INC
Category: otc | Type: HUMAN OTC DRUG LABEL
Date: 20171220

ACTIVE INGREDIENTS: BENZALKONIUM CHLORIDE .13 1/1 1; BENZALKONIUM CHLORIDE .13 1/1 1; BENZALKONIUM CHLORIDE .13 1/1 1
INACTIVE INGREDIENTS: water; grapefruit; polysorbate 20; .ALPHA.-TOCOPHEROL ACETATE; ALOE VERA LEAF; PHENOXYETHANOL; ANHYDROUS CITRIC ACID; Water; PEPPERMINT OIL; POLYSORBATE 20; SPEARMINT OIL; ALOE VERA LEAF; PHENOXYETHANOL; ANHYDROUS CITRIC ACID; .ALPHA.-TOCOPHEROL ACETATE, DL-; Water; LAVENDER OIL; POLYSORBATE 20; ALOE VERA LEAF; PHENOXYETHANOL; ANHYDROUS CITRIC ACID; .ALPHA.-TOCOPHEROL ACETATE, DL-

Mixed Packaging

Active Ingredient

Benzalkonium Chloride 0.13%

Purpose

Antimicrobial

Uses

For hand sanitizing to decrease bacteria on the skin

Directions

Open packet, unfold and rub thoroughly over hand

Warnings

For external use only.
When using this product avoid contact with eyes.
If irritation and redness develop and lasts, stop using this product and ask a doctor.

Keep Out Of Reach Of Children

If swallowed, get medical help or contact a Poison Control Center right away

Inactive Ingredients

Grapefruit SplashTM: Aloe Barbadensis Leaf Juice, Citric Acid, Citrus Grandis (Grapefruit) Peel Oil, Phenoxyethanol, Polysorbate 20, Tocopheryl Acetate (Vitamin E Acetate), Water Lavender CalmTM: Aloe Barbadensis Leaf Juice, Citric Acid, Lavandula Angustifolia (Lavender) Oil, Phenoxyethanol, Polysorbate 20, Tocopheryl Acetate (Vitamin E Acetate), Water Peppermint SurgeTM: Aloe Barbadensis Leaf Juice, Citric Acid, Mentha Piperita (Peppermint) Oil, Mentha Virdis (Spearmint) Leaf Oil, Phenoxyethanol, Polysorbate 20, Tocopheryl Acetate (Vitamin E Acetate), Water

Questions

1-800-563-5458 Monday thru Friday 8:00 AM - 5:00 PM PST